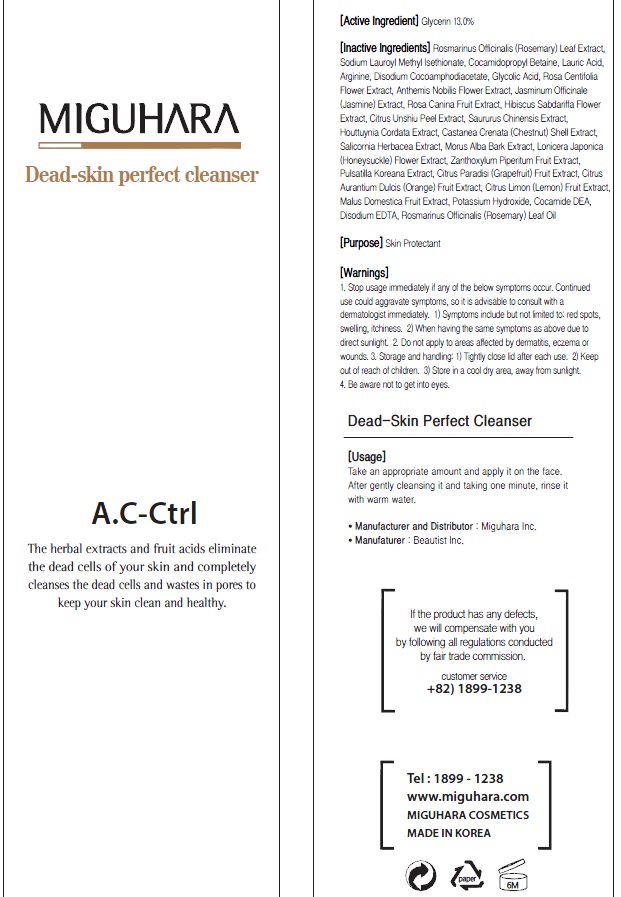 DRUG LABEL: Dead Skin Perfect Cleanser
NDC: 70380-170 | Form: LIQUID
Manufacturer: MIGUHARA
Category: otc | Type: HUMAN OTC DRUG LABEL
Date: 20160222

ACTIVE INGREDIENTS: Glycerin 26 g/200 mL
INACTIVE INGREDIENTS: ROSEMARY; Cocamidopropyl Betaine

ACTIVE INGREDIENT

Active Ingredient: Glycerin 13.0%

INACTIVE INGREDIENT

Inactive Ingredients: Rosmarinus Officinalis (Rosemary) Leaf Extract, Sodium Lauroyl Methyl Isethionate, Cocamidopropyl Betaine, Lauric Acid, Arginine, Disodium Cocoamphodiacetate, Glycolic Acid, Rosa Centifolia Flower Extract, Anthemis Nobilis Flower Extract, Jasminum Officinale (Jasmine) Extract, Rosa Canina Fruit Extract, Hibiscus Sabdariffa Flower Extract, Citrus Unshiu Peel Extract, Saururus Chinensis Extract, Houttuynia Cordata Extract, Castanea Crenata (Chestnut) Shell Extract, Salicornia Herbacea Extract, Morus Alba Bark Extract, Lonicera Japonica (Honeysuckle) Flower Extract, Zanthoxylum Piperitum Fruit Extract, Pulsatilla Koreana Extract, Citrus Paradisi (Grapefruit) Fruit Extract, Citrus Aurantium Dulcis (Orange) Fruit Extract, Citrus Limon (Lemon) Fruit Extract, Malus Domestica Fruit Extract, Potassium Hydroxide, Cocamide DEA, Disodium EDTA, Rosmarinus Officinalis (Rosemary) Leaf Oil

PURPOSE

Purpose: Skin Protectant

WARNINGS

1. Stop usage immediately if any of the below symptoms occur. Continued use could aggravate symptoms, so it is advisable to consult with a dermatologist immediately. 1) Symptoms include but not limited to: red spots, swelling, itchiness. 2) When having the same symptoms as above due to direct sunlight. 2. Do not apply to areas affected by dermatitis, eczema or wounds. 3. Storage and handling: 1) Tightly close lid after each use. 2 Keep out of reach of children 3) Store in a cool dry area, away from sunlight 4. Be aware not to get into eyes.

KEEP OUT OF REACH OF CHILDREN

Usage

Usage: Take an appropriate amount and apply it on the face. After gently cleansing it and taking one minute, rinse it with warm water.

Usage

Usage: Take an appropriate amount and apply it on the face. After gently cleansing it and taking one minute, rinse it with warm water.